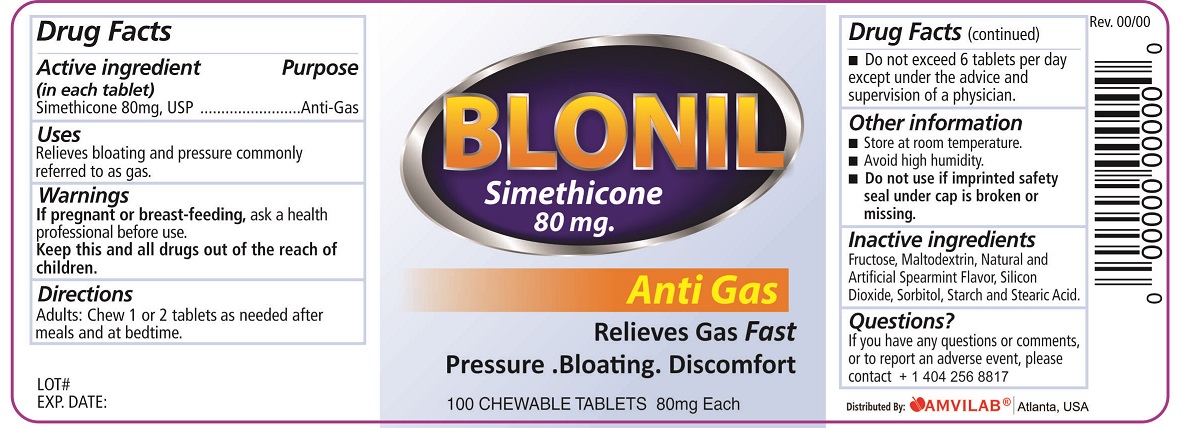 DRUG LABEL: Blonil
NDC: 69975-870 | Form: TABLET, CHEWABLE
Manufacturer: Amvilab LLC
Category: otc | Type: HUMAN OTC DRUG LABEL
Date: 20150716

ACTIVE INGREDIENTS: DIMETHICONE 80 mg/1 1
INACTIVE INGREDIENTS: FRUCTOSE; MALTODEXTRIN; SILICON DIOXIDE; SORBITOL; STARCH, CORN; STEARIC ACID

Drug Facts

Active ingredient (in each tablet)

Simethicone 80 mg, USP

Purpose

Anti-Gas

Uses

Relieves bloating and pressure commonly referred to as gas.

Warnings

PREGNANCY OR BREAST FEEDING

If pregnant or breast-feeding, ask a health professional before use.

Directions

- Adults: Chew 1 or 2 tablets as needed after meals and at bedtime.
- Do not exceed 6 tablets per day except under the advice and supervision of a physician.

Other Information

- Store at room temperature.
- Avoid high humidity.
- Do not use if imprinted safety seal under cap is broken or missing.

Inactive ingredients

Fructose, Maltodextrin, Natural and Artificial Spearmint Flavor, Silicon Dioxide, Sorbitol, Starch and Stearic Acid.

Questions?

If you have any questions or comments, or to report an adverse event, please contact +1 404 256 8817.

Principal Display Panel

BLONIL

Simethicone 80 mg

Anti Gas

Relieves Gas Fast

- Pressure
- Bloating
- Discomfort

100 CHEWABLE TABLETS 80mg Each